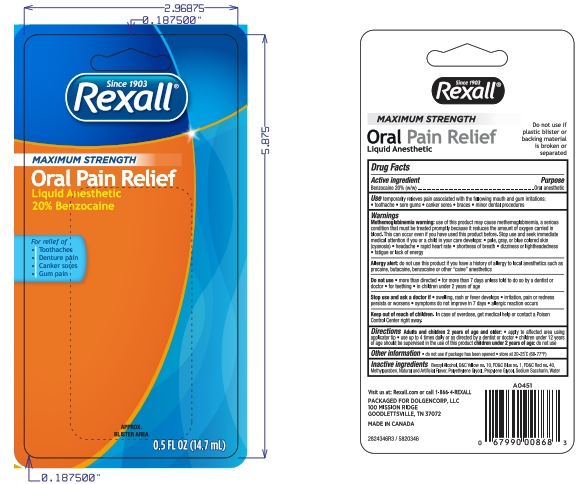 DRUG LABEL: Rexall
NDC: 55910-346 | Form: LIQUID
Manufacturer: Rexall
Category: otc | Type: HUMAN OTC DRUG LABEL
Date: 20250812

ACTIVE INGREDIENTS: BENZOCAINE 20 g/100 mL
INACTIVE INGREDIENTS: POLYETHYLENE GLYCOL 400; PROPYLENE GLYCOL; SACCHARIN SODIUM; METHYLPARABEN; BENZYL ALCOHOL; FD&C RED NO. 40; D&C YELLOW NO. 10; FD&C BLUE NO. 1

5820346 DG Max Str OP Relief Liq

Active ingredient

Benzocaine 20.0% ..................................Purpose: Oral pain reliever

Uses

Temporarily relieves pain associated with the following mouth irritations toothache sore gums canker sores braces minor dental procedures

Allergy alert: do not use this product if you have a history of allergy to local anesthetics such as procaine, butacaine, benzocaine or other “caine” anesthetics

When using this product

- avoid contact with eyes
- do not exceed recommended dosage
- Do not use more than directed for more than 7 days unless directed by a dentist or doctor.

Stop use and ask a doctor if sore mouth symptoms do not improve in 7 days, swelling, rash or fever develops, irritation, pain or redness persists or worsens swelling rash or fever developes

Keep out of reach of children. In case of overdose, get medical help or contact a Poison Control Center right away.

Directions

Adults and children 2 years of age and older:

- apply to affect4ed area using applicator tip
- use up to 4 times daily or as directed by a dentist or doctor.
- Children under 12 years of age should be supervised in the use of this product.

Children under 2 years of age: ask a dentist or doctor.

Other Information

Do not use if package has been opened

Store at 20-25°C (68-77°F)

Inactive ingredients

Benzyl Alcohol, D&C Yellow 10, FD&C Blue 1, FD&C Red 40, FD&C Yellow 5, Methylparaben, Flavor, Polyethylene Glycol, Propylene Glycol, Sodium Saccharin, Water

DOSAGE AND ADMINISTRATION

Adults and children 2 years of age and older:
apply to affect4ed area using applicator tip
use up to 4 times daily or as directed by a dentist or doctor.
Children under 12 years of age should be supervised in the use of this product.
Children under 2 years of age: ask a dentist or doctor.